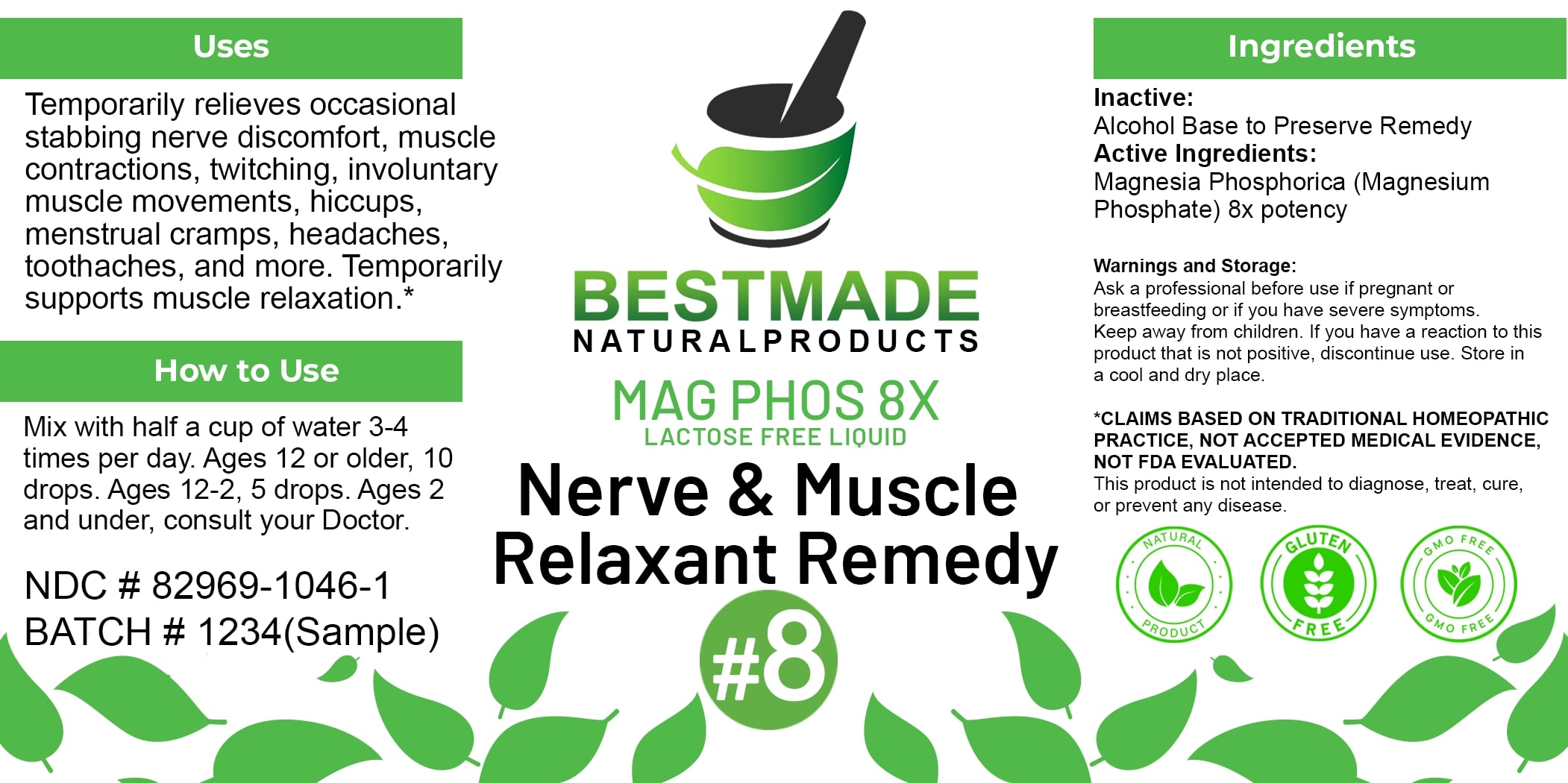 DRUG LABEL: Bestmade Natural Products Mag Phos 8x
NDC: 82969-1046 | Form: LIQUID
Manufacturer: Bestmade Natural Products
Category: homeopathic | Type: HUMAN OTC DRUG LABEL
Date: 20250403

ACTIVE INGREDIENTS: MAGNESIUM PHOSPHATE, DIBASIC TRIHYDRATE 8 [hp_X]/8 [hp_X]
INACTIVE INGREDIENTS: ALCOHOL 8 [hp_X]/8 [hp_X]

Mag Phos 8x - liquid lactose free

DOSAGE AND ADMINISTRATION

How to Use

Mix with half a cup of water 3-4 times per day. Ages 12 or older, 10 drops. Ages 12-2, 5 drops. Ages 2 and under, consult your Doctor.

Inactive:

Alcohol Base to Preserve Product

Active Ingredients:
Magnesia Phosphorica (Magnesium Phosphate) 8x potency

Uses

Temporarily relieves occasional stabbing nerve discomfort, muscle contractions, twitching, involuntary muscle movements, hiccups, menstrual cramps, headaches, toothaches, and more. Temporarily supports muscle relaxation.*

*CLAIMS BASED ON TRADITIONAL HOMEOPATHIC PRACTICE, NOT ACCEPTED MEDICAL EVIDENCE NOT FDA EVALUATED.

This product is not intended to diagnose, treat, cure, or prevent any disease.

Uses

Temporarily relieves occasional stabbing nerve discomfort, muscle contractions, twitching, involuntary muscle movements, hiccups, menstrual cramps, headaches, toothaches, and more. Temporarily supports muscle relaxation.*

*CLAIMS BASED ON TRADITIONAL HOMEOPATHIC PRACTICE, NOT ACCEPTED MEDICAL EVIDENCE NOT FDA EVALUATED.

This product is not intended to diagnose, treat, cure, or prevent any disease.

KEEP OUT OF REACH OF CHILDREN

Warnings and Storage:

Ask a professional before use if pregnant or breastfeeding or if you have severe symptoms. Keep away from children. If you have a reaction to this product that is not positive, discontinue use. Store in a cool and dry place

Warnings and Storage:

Ask a professional before use if pregnant or breastfeeding or if you have severe symptoms. Keep away from children. If you have a reaction to this product that is not positive, discontinue use. Store in a cool and dry place.

*CLAIMS BASED ON TRADITIONAL HOMEOPATHIC PRACTICE, NOT ACCEPTED MEDICAL EVIDENCE NOT FDA EVALUATED.

This product is not intended to diagnose, treat, cure, or prevent any disease.

Entire package label